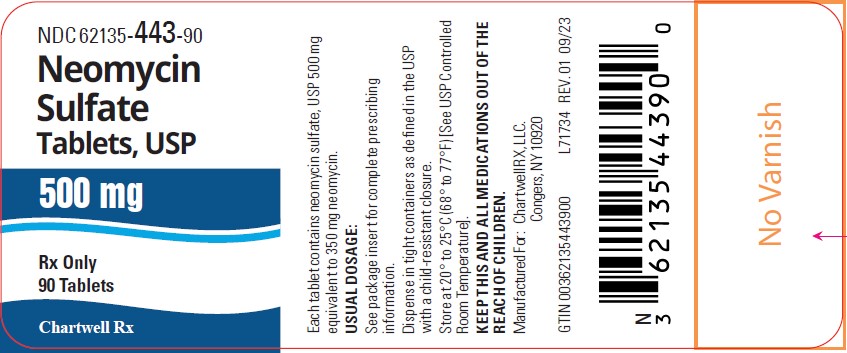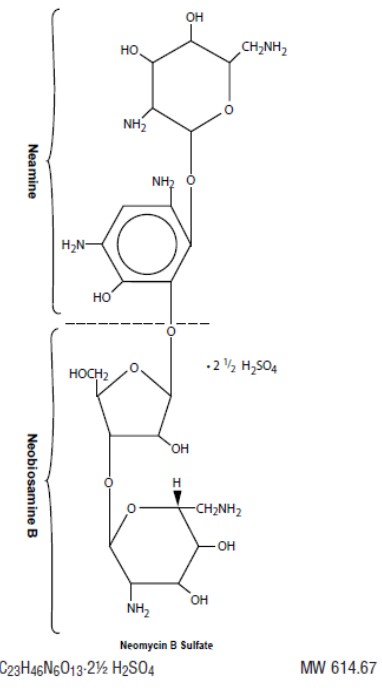 DRUG LABEL: Neomycin Sulfate
NDC: 62135-443 | Form: TABLET
Manufacturer: Chartwell RX, LLC
Category: prescription | Type: HUMAN PRESCRIPTION DRUG LABEL
Date: 20260227

ACTIVE INGREDIENTS: NEOMYCIN SULFATE 500 mg/1 1
INACTIVE INGREDIENTS: CALCIUM STEARATE; POVIDONE K30; ANHYDROUS LACTOSE

Neomycin Sulfate Tablets, USP
RX ONLY

To reduce the development of drug-resistant bacteria and maintain the effectiveness of neomycin sulfate tablets and other antibacterial drugs, neomycin sulfate tablets should be used only to treat or prevent infections that are proven or strongly suspected to be caused by bacteria.

WARNINGS

SYSTEMIC ABSORPTION OF NEOMYCIN OCCURS FOLLOWING ORAL ADMINISTRATION AND TOXIC REACTIONS MAY OCCUR. Patients treated with neomycin should be under close clinical observation because of the potential toxicity associated with their use. NEUROTOXICITY (INCLUDING OTOTOXICITY) AND NEPHROTOXICITY FOLLOWING THE ORAL USE OF NEOMYCIN SULFATE HAVE BEEN REPORTED, EVEN WHEN USED IN RECOMMENDED DOSES. THE POTENTIAL FOR NEPHROTOXICITY, PERMANENT BILATERAL AUDITORY OTOTOXICITY AND SOMETIMES VESTIBULAR TOXICITY IS PRESENT IN PATIENTS WITH NORMAL RENAL FUNCTION WHEN TREATED WITH HIGHER DOSES OF NEOMYCIN AND/OR FOR LONGER PERIODS THAN RECOMMENDED. Serial, vestibular and audiometric tests, as well as tests of renal function, should be performed (especially in high-risk patients). THE RISK OF NEPHROTOXICITY AND OTOTOXICITY IS GREATER IN PATIENTS WITH IMPAIRED RENAL FUNCTION. Ototoxicity is often delayed in onset and patients developing cochlear damage will not have symptoms during therapy to warn them of developing eighth nerve destruction and total or partial deafness may occur long after neomycin has been discontinued.

Neuromuscular blockage and respiratory paralysis have been reported following the oral use of neomycin. The possibility of the occurrence of neuromuscular blockage and respiratory paralysis should be considered if neomycin is administered, especially to patients receiving anesthetics, neuromuscular blocking agents such as tubocurarine, succinylcholine, decamethonium, or in patients receiving massive transfusions of citrate anticoagulated blood. If blockage occurs, calcium salts may reverse these phenomena but mechanical respiratory assistance may be necessary.

Concurrent and/or sequential systemic, oral or topical use of other aminoglycosides, including paromomycin and other potentially nephrotoxic and/or neurotoxic drugs such as bacitracin, cisplatin, vancomycin, amphotericin B, polymyxin B, colistin and viomycin, should be avoided because the toxicity may be additive.

Other factors which increase the risk of toxicity are advanced age and dehydration.

The concurrent use of neomycin with potent diuretics such as ethacrynic acid or furosemide should be avoided, since certain diuretics by themselves may cause ototoxicity. In addition, when administered intravenously, diuretics may enhance neomycin toxicity by altering the antibiotic concentration in serum and tissue.

DESCRIPTION

Neomycin Sulfate Tablets, USP for oral administration, contain neomycin which is an antibiotic obtained from the metabolic products of the actinomycete Streptomyces fradiae.

Structurally, Neomycin Sulfate, USP may be represented as follows:

Chemically, it is O-2,6-diamino-2,6-dideoxy-α-D- glucopyranosyl-(1→3)- O-β-D-ribofuranosyl-(1→ 5)- O- [2,6-diamino-2,6-dideoxy -α-D- glucopyranosyl-(1→ 4)]-2-deoxy-D-streptamine. Neomycin B is identical except that the α -D- glucopyranosyl residue in the neobiosamine moiety is β-L-idopyranosyl.

Each tablet contains 500 mg Neomycin Sulfate, USP (equivalent to 350 mg neomycin base).

Inactive Ingredients:anhydrous lactose, calcium stearate, and povidone.

CLINICAL PHARMACOLOGY

Neomycin sulfate is poorly absorbed from the normal gastrointestinal tract. The small absorbed fraction is rapidly distributed in the tissues and is excreted by the kidney in keeping with the degree of kidney function. The unabsorbed portion of the drug (approximately 97%) is eliminated unchanged in the feces.

Growth of most intestinal bacteria is rapidly suppressed following oral administration of neomycin sulfate, with the suppression persisting for 48 to 72 hours. Nonpathogenic yeasts and occasionally resistant strains of Enterobacter aerogenes(formerly Aerobacter aerogenes) replace the intestinal bacteria.

As with other aminoglycosides, the amount of systemically absorbed neomycin transferred to the tissues increases cumulatively with each repeated dose administered until a steady state is achieved. The kidney functions as the primary excretory path as well as the tissue binding site, with the highest concentration found in the renal cortex. With repeated dosings, progressive accumulation also occurs in the inner ear. Release of tissue-bound neomycin occurs slowly over a period of several weeks after dosing has been discontinued.

Protein binding studies have shown that the degree of aminoglycoside protein binding is low and, depending upon the methods used for testing, this may be between 0% and 30%.

Microbiology

In vitro tests have demonstrated that neomycin is bactericidal and acts by inhibiting the synthesis of protein in susceptible bacterial cells. It is effective primarily against gram-negative bacilli but does have some activity against gram-positive organisms. Neomycin is active in vitroagainst Escherichia coliand the Klebsiella- Enterobactergroup. Neomycin is not active against anaerobic bowel flora.

Susceptibility Testing

For specific information regarding susceptibility test interpretive criteria and associated test methods and quality control standards recognized by FDA for this drug, please see: https://www.fda.gov/STIC.

INDICATIONS AND USAGE

To reduce the development of drug-resistant bacteria and maintain the effectiveness of neomycin sulfate tablets and other antibacterial drugs, neomycin sulfate tablets should be used only to treat or prevent infections that are proven or strongly suspected to be caused by susceptible bacteria. When culture and susceptibility information are available, they should be considered in selecting or modifying antibacterial therapy. In the absence of such data, local epidemiology and susceptibility patterns may contribute to the empiric selection of therapy.

Suppression of Intestinal Bacteria

Neomycin sulfate tablets are indicated as adjunctive therapy as part of a regimen for the suppression of the normal bacterial flora of the bowel, e.g., preoperative preparation of the bowel. It is given concomitantly with erythromycin enteric-coated base (see DOSAGE AND ADMINISTRATION).

Hepatic Coma (Portal-Systemic Encephalopathy)

Neomycin sulfate has been shown to be effective adjunctive therapy in hepatic coma by reduction of the ammonia-forming bacteria in the intestinal tract. The subsequent reduction in blood ammonia has resulted in neurologic improvement.

CONTRAINDICATIONS

Neomycin sulfate oral preparations are contraindicated in the presence of intestinal obstruction and in individuals with a history of hypersensitivity to the drug. Patients with a history of hypersensitivity or serious toxic reaction to other aminoglycosides may have a cross-sensitivity to neomycin.

Neomycin sulfate oral preparations are contraindicated in patients with inflammatory or ulcerative gastro- intestinal disease because of the potential for enhanced gastrointestinal absorption of neomycin.

WARNINGS (SEE BOXED WARNINGS)

Additional manifestations of neurotoxicity may include numbness, skin tingling, muscle twitching and convulsions.

The risk of hearing loss continues after drug withdrawal.

Aminoglycosides can cause fetal harm when administered to a pregnant woman. Aminoglycoside antibiotics cross the placenta and there have been several reports of total irreversible bilateral congenital deafness in children whose mothers received streptomycin during pregnancy. Although serious side effects to fetus or newborn have not been reported in the treatment of pregnant women with other aminoglycosides, the potential for harm exists. Animal reproduction studies of neomycin have not been conducted. If neomycin is used during pregnancy, or if the patient becomes pregnant while taking this drug, the patient should be apprised of the potential hazard to the fetus.

Risk of Ototoxicity Due to Mitochondrial DNA Variants

Cases of ototoxicity with aminoglycosides have been observed in patients with certain variants in the mitochondrially encoded 12S rRNA gene (MT-RNR1), particularly the m.1555A>G variant. Ototoxicity occurred in some patients even when their aminoglycoside serum levels were within the recommended range. Mitochondrial DNA variants are present in less than 1% of the general US population, and the proportion of the variant carriers who may develop ototoxicity as well as the severity of ototoxicity is unknown. In case of known maternal history of ototoxicity due to aminoglycoside use or a known mitochondrial DNA variant in the patient, consider alternative treatments other than aminoglycosides unless the increased risk of permanent hearing loss is outweighed by the severity of infection and lack of safe and effective alternative therapies.

PRECAUTIONS

General

Prescribing neomycin sulfate tablets in the absence of a proven or strongly suspected bacterial infection or a prophylactic indication is unlikely to provide benefit to the patient and increases the risk of the development of drug-resistant bacteria.

As with other antibiotics, use of oral neomycin may result in overgrowth of nonsusceptible organisms, particularly fungi. If this occurs, appropriate therapy should be instituted.

Neomycin is quickly and almost totally absorbed from body surfaces (except the urinary bladder) after local irrigation and when applied topically in association with surgical procedures. Delayed-onset irreversible deafness, renal failure and death due to neuromuscular blockade (regardless of the status of renal function) have been reported following irrigation of both small and large surgical fields with minute quantities of neomycin.

Cross-allergenicity among aminoglycosides has been demonstrated.

Aminoglycosides should be used with caution in patients with muscular disorders such as myasthenia gravis or parkinsonism since these drugs may aggravate muscle weakness because of their potential curare-like effect on the neuromuscular junction.

Small amounts of orally administered neomycin are absorbed through intact intestinal mucosa.

There have been many reports in the literature of nephrotoxicity and/or ototoxicity with oral use of neomycin. If renal insufficiency develops during oral therapy, consideration should be given to reducing the drug dosage or discontinuing therapy.

An oral neomycin dose of 12 grams per day produces a malabsorption syndrome for a variety of substances, including fat, nitrogen, cholesterol, carotene, glucose, xylose, lactose, sodium, calcium, cyanocobalamin and iron.

Orally administered neomycin increases fecal bile acid excretion and reduces intestinal lactase activity.

Information for Patients

Patients should be counseled that antibacterial drugs including neomycin sulfate tablets should only be used to treat bacterial infections. They do not treat viral infections (e.g., the common cold). When neomycin sulfate tablets are prescribed to treat a bacterial infection, patients should be told that although it is common to feel better early in the course of therapy, the medication should be taken exactly as directed. Skipping doses or not completing the full course of therapy may (1) decrease the effectiveness of the immediate treatment and (2) increase the likelihood that bacteria will develop resistance and will not be treatable by neomycin sulfate tablets or other antibacterial drugs in the future.

Before administering the drug, patients or members of their families should be informed of possible toxic effects on the eighth nerve. The possibility of acute toxicity increases in premature infants and neonates.

Laboratory Tests

Patients with renal insufficiency may develop toxic neomycin blood levels unless doses are properly regulated. If renal insufficiency develops during treatment, the dosage should be reduced or the antibiotic discontinued. To avoid nephrotoxicity and eighth nerve damage associated with high doses and prolonged treatment, the following should be performed prior to and periodically during therapy: urinalysis for increased excretion of protein, decreased specific gravity, casts and cells; renal function tests such as serum creatinine, BUN or creatinine clearance; tests of the vestibulocochlearis nerve (eighth cranial nerve) function.

Serial, vestibular and audiometric tests should be performed (especially in high-risk patients). Since elderly patients may have reduced renal function which may not be evident in the results of routine screening tests such as BUN or serum creatinine, a creatinine clearance determination may be more useful.

Drug Interactions

Caution should be taken in concurrent or serial use of other neurotoxic and/or nephrotoxic drugs because of possible enhancement of the nephrotoxicity and/or ototoxicity of neomycin (see BOXED WARNINGS).

Caution should also be taken in concurrent or serial use of other aminoglycosides and polymyxins because they may enhance neomycin’s nephrotoxicity and/or ototoxicity and potentiate neomycin sulfate’s neuromuscular blocking effects.

Oral neomycin inhibits the gastrointestinal absorption of penicillin V, oral vitamin B-12, methotrexate and 5-fluorouracil. The gastrointestinal absorption of digoxin also appears to be inhibited. Therefore, digoxin serum levels should be monitored.

Oral neomycin sulfate may enhance the effect of coumarin in anticoagulants by decreasing vitamin K availability.

Carcinogenesis, Mutagenesis, Impairment of Fertility

No long-term animal studies have been performed with neomycin sulfate to evaluate carcinogenic or mutagenic potential or impairment of fertility.

Pregnancy

See WARNINGSsection.

Nursing Mothers

It is not known whether neomycin is excreted in human milk, but it has been shown to be excreted in cow milk following a single intramuscular injection. Other aminoglycosides have been shown to be excreted in human milk. Because of the potential for serious adverse reactions from the aminoglycosides in nursing infants, a decision should be made whether to discontinue nursing or to discontinue the drug, taking into account the importance of the drug to the mother.

Pediatric Use

The safety and efficacy of oral neomycin sulfate in patients less than 18 years of age have not been established. If treatment of a patient less than 18 years of age is necessary, neomycin should be used with caution and the period of treatment should not exceed two weeks because of absorption from the gastrointestinal tract.

ADVERSE REACTIONS

The most common adverse reactions to oral neomycin sulfate are nausea, vomiting and diarrhea. The “Malabsorption Syndrome” characterized by increased fecal fat, decreased serum carotene and fall in xylose absorption has been reported with prolonged therapy. Nephrotoxicity, ototoxicity and neuromuscular blockage have been reported (see BOXED WARNINGS and PRECAUTIONSsections).

OVERDOSAGE

Because of low absorption, it is unlikely that acute overdosage would occur with oral neomycin sulfate. However, prolonged administration could result in sufficient systemic drug levels to produce neurotoxicity, ototoxicity and/or nephrotoxicity.

Hemodialysis will remove neomycin sulfate from the blood.

DOSAGE AND ADMINISTRATION

To minimize the risk of toxicity, use the lowest possible dose and the shortest possible treatment period to control the condition. Treatment for periods longer than two weeks is not recommended.

Hepatic Coma

For use as an adjunct in the management of hepatic coma, the recommended dose is 4 to 12 grams per day given in the following regimen:

1. Withdraw protein from diet. Avoid use of diuretic agents.
2. Give supportive therapy, including blood products, as indicated.
3. Give neomycin sulfate tablets in doses of 4 to 12 grams of neomycin sulfate per day (eight to 24 tablets) in divided doses. Treatment should be continued over a period of five to six days, during which time protein should be returned incrementally to the diet.
4. If less potentially toxic drugs cannot be used for chronic hepatic insufficiency, neomycin in doses of up to four grams daily (eight tablets per day) may be necessary. The risk for the development of neomycin-induced toxicity progressively increases when treatment must be extended to preserve the life of a patient with hepatic encephalopathy who has failed to fully respond. Frequent periodic monitoring of these patients to ascertain the presence of drug toxicity is mandatory (see PRECAUTIONS). Also, neomycin serum concentrations should be monitored to avoid potentially toxic levels. The benefits to the patient should be weighed against the risks of nephrotoxicity, permanent ototoxicity and neuromuscular blockade following the accumulation of neomycin in the tissues.

Preoperative Prophylaxis for Elective Colorectal Surgery.

Listed below is an example of a recommended bowel preparation regimen. A proposed surgery time of 8:00 a.m. has been used.

Pre-op Day 3:Minimum residue or clear liquid diet. Bisacodyl, 1 tablet orally at 6:00 p.m.

Pre-op Day 2:Minimum residue or clear liquid diet. Magnesium sulfate, 30 mL, 50% solution (15 g) orally at 10:00 a.m., 2:00 p.m., and 6:00 p.m. Enema at 7:00 p.m. and 8:00 p.m.

Pre-op Day 1:Clear liquid diet. Supplemental (IV) fluids as needed. Magnesium sulfate, 30 mL, 50% solution (15 g) orally at 10:00 a.m., and 2:00 p.m. Neomycin sulfate (1 g) and erythromycin base (1 g) orally at 1:00 p.m., 2:00 p.m. and 11:00 p.m. No enema.

Day of Operation:Patient evacuates rectum at 6:30 a.m. for scheduled operation at 8:00 a.m.

HOW SUPPLIED

Neomycin Sulfate Tablets, USP 500 mg (equivalent to 350 mg of neomycin base per tablet) are available as white to off-white, round tablets debossed with “ CE” on one side and “ 119”, on the other side and are supplied in:

Bottles of 90 (NDC 62135-443-90)

Store at 20° to 25°C (68° to 77°F) [See USP Controlled Room Temperature].

Dispense in tight containers as defined in the USP/NF.

KEEP THIS AND ALL MEDICATIONS OUT OF THE REACH OF CHILDREN.

Manufactured for
Chartwell RX, LLC.
Congers, NY 10920

L71735

Rev. 02/2026

PACKAGE LABEL.PRINCIPAL DISPLAY PANEL

Neomycin Sulfate Tablets, USP 500 mg - NDC 62135-443-90 - 90's Bottle Label